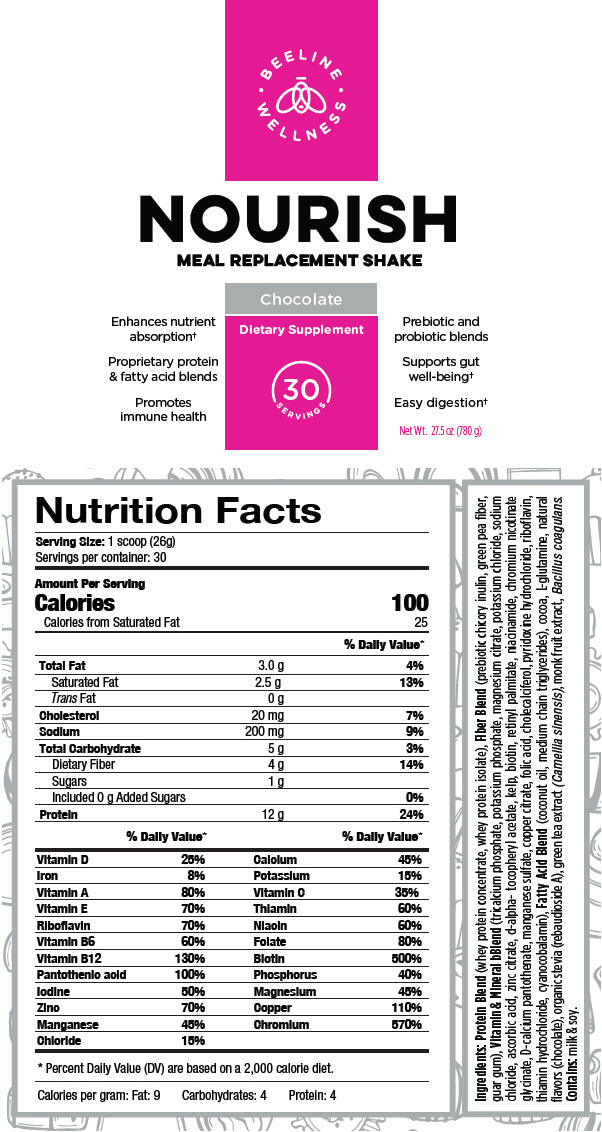 DRUG LABEL: Nourish
NDC: 69833-060 | Form: POWDER, FOR SOLUTION
Manufacturer: Spring Hill Therapeutics LLC
Category: other | Type: DIETARY SUPPLEMENT
Date: 20200903

ACTIVE INGREDIENTS: Whey Protein Hydrolysate 12 g/26 g
INACTIVE INGREDIENTS: Vitamin D; Iron; Vitamin A; .Alpha.-Tocopherol; Riboflavin; Pyridoxine; Cyanocobalamin; Pantothenic Acid; Iodine; Zinc; Manganese; Chloride Ion; Calcium; Potassium; Ascorbic Acid; Thiamine; Niacin; Folic Acid; Biotin; Phosphorus; Magnesium; Copper; Chromium; Whey; Guar Gum; tricalcium phosphate; potassium phosphate, unspecified form; magnesium citrate; potassium chloride; sodium chloride; zinc citrate; vitamin A palmitate; niacinamide; calcium pantothenate; manganese sulfate; cupric citrate; cholecalciferol; pyridoxine hydrochloride; thiamine hydrochloride; coconut oil; medium-chain triglycerides; cocoa; glutamine; rebaudioside A; green tea leaf; Bacillus coagulans; cow milk

NOURISH MEAL REPLACEMENT SHAKE

STATEMENT OF IDENTITY

Nutrition Facts
Serving Size: 1 scoop (26g)
Servings per container: 30
Amount Per Serving
Calories |  |  | 100
Calories from Saturated Fat |  |  | 25
% Daily Value [Percent Daily Value (DV) are based on a 2,000 calorie diet.]
Total Fat | 3.0 g |  | 4%
Saturated Fat | 2.5 g |  | 13%
Trans Fat | 0 g
Cholesterol | 20 mg |  | 7%
Sodium | 200 mg |  | 9%
Total Carbohydrate | 5 g |  | 3%
Dietary Fiber | 4 g |  | 14%
Sugars | 1 g
Included 0 g Added Sugars |  |  | 0%
Protein | 12 g |  | 24%
 | % Daily Value |  |  | % Daily Value
Vitamin D | 25% |  | Calcium | 45%
Iron | 8% |  | Potassium | 15%
Vitamin A | 80% |  | Vitamin C | 35%
Vitamin E | 70% |  | Thiamin | 60%
Riboflavin | 70% |  | Niacin | 60%
Vitamin B6 | 60% |  | Folate | 80%
Vitamin B12 | 130% |  | Biotin | 500%
Pantothenic acid | 100% |  | Phosphorus | 40%
Iodine | 50% |  | Magnesium | 45%
Zinc | 70% |  | Copper | 110%
Manganese | 45% |  | Chromium | 570%
Chloride | 15%
Calories per gram: Fat: 9 Carbohydrates: 4 Protein: 4

Ingredients: Protein Blend (whey protein concentrate, whey protein isolate), Fiber Blend (prebiotic chicory inulin, green pea fiber, guar gum), Vitamin & Mineral bBlend (tricalcium phosphate, potassium phosphate, magnesium citrate, potassium chloride, sodium chloride, ascorbic acid, zinc citrate, d-alpha- tocopheryl acetate, kelp, biotin, retinyl palmitate, niacinamide, chromium nicotinate glycinate, D-calcium pantothenate, manganese sulfate, copper citrate, folic acid, cholecalciferol, pyridoxine hydrochloride, riboflavin, thiamin hydrochloride, cyanocobalamin), Fatty Acid Blend (coconut oil, medium chain triglycerides), cocoa, L-glutamine, natural flavors (chocolate), organic stevia (rebaudioside A), green tea extract (Camellia sinensis), monk fruit extract, Bacillus coagulans.

Contains: milk & soy.

PRINCIPAL DISPLAY PANEL - 780 g Canister Label

BEELINE
WELLNESS

NOURISH
MEAL REPLACEMENT SHAKE

Chocolate

Enhances nutrient
absorption†

Proprietary protein
& fatty acid blends

Promotes
immune health

Dietary Supplement

30
SERVINGS

Prebiotic and
probiotic blends

Supports gut
well-being†

Easy digestion†

Net Wt. 27.5 oz (780 g)